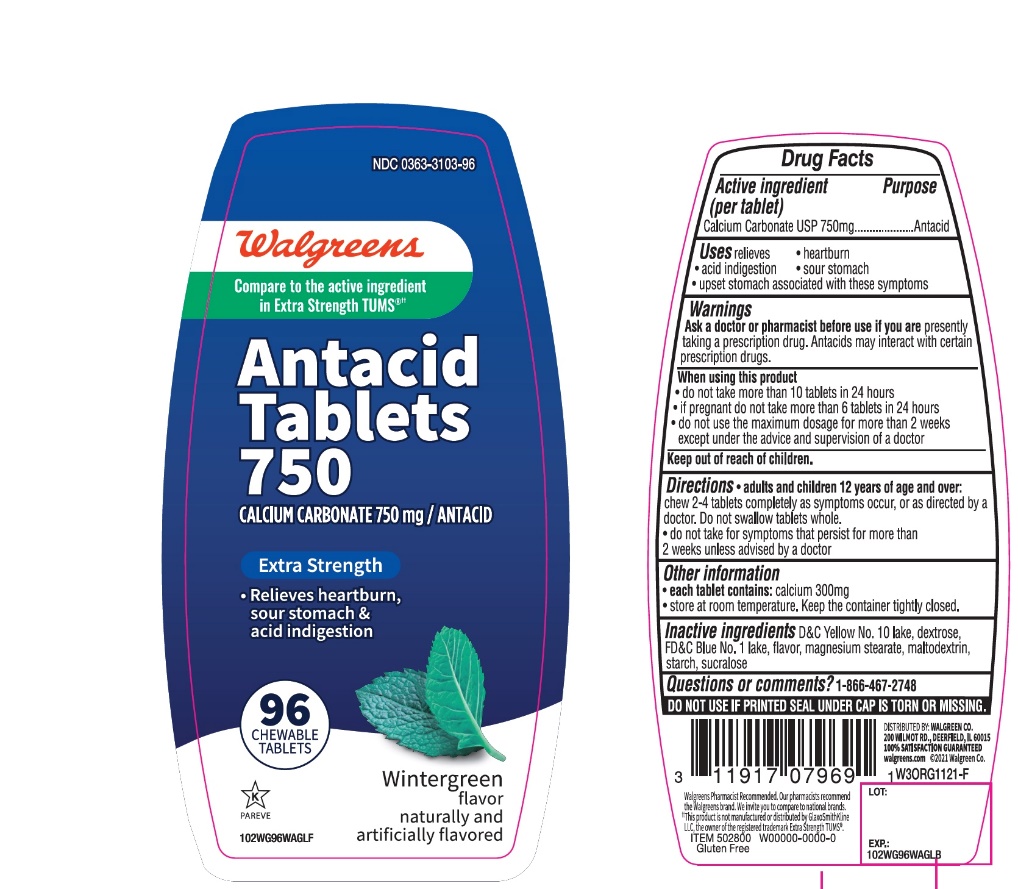 DRUG LABEL: Antacid Extra Strength

NDC: 0363-3103 | Form: TABLET, CHEWABLE
Manufacturer: WALGREEN CO.
Category: otc | Type: HUMAN OTC DRUG LABEL
Date: 20251125

ACTIVE INGREDIENTS: CALCIUM CARBONATE 750 mg/1 1
INACTIVE INGREDIENTS: D&C YELLOW NO. 10; DEXTROSE, UNSPECIFIED FORM; FD&C BLUE NO. 1; MAGNESIUM STEARATE; MALTODEXTRIN; STARCH, CORN; SUCRALOSE

Walgreens Antacid Calcium Carbonate 750mg Extra Strength Wintergreen 96 Chewable Tablets

Active ingredient (per tablet)

Calcium Carbonate USP 750 mg

Purpose

Antacid

Uses

relieves:

- heartburn
- sour stomach
- acid indigestion
- upset stomach associated with these symptoms

Warnings

Ask a doctor or pharmacist before use if you arepresently taking a prescription drug. Antacids may interact with certain prescription drugs.

When using this product

- do not take more than 10 tablets in 24 hours
- if pregnant do not take more than 6 tablets in 24 hours
- do not use the maximum dosage for more than 2 weeks except under the advice and supervision of a doctor

Directions

- adults and children 12 years of age and older:chew 2-4 tablets completely as symptoms occur, or as directed by a doctor. Do not swallow tablets whole.
- do not take for symptoms that persist for more than 2 weeks unless advised by a doctor

Other information

- each tablet contains:elemental calcium 300mg
- store at room temperature. Keep the container tightly closed.

Inactive ingredients

D&C Yellow No. 10, dextrose, FD&C Blue No. 1, flavor, magnesium stearate, maltodextrin, starch, sucralose

Questions or comments?

1-866-467-2748

SAFETY SEALED: DO NOT USE IF PRINTED SEAL UNDER CAP IS TORN OR MISSING

Package/Label Principal Display Panel

Walgreens

Compare to TUMS®active ingredients††

Antacid Tablets 750

CALCIUM CARBONATE 750 mg/ ANTACID

EXTRA STRENGTH

- Relieves heartburn, sour stomach & acid indigestion

WINTERGREEN FLAVOR

96 CHEWABLE TABLETS

GLUTEN-FREE

Walgreens Pharmacist Recommended

Walgreens Pharmacist Survey

DISTRIBUTED BY: WALGREEN CO.

200 WILMOT RD., DEERFIELD, IL 60015

100 % SATISFACTION GUARANTEED

walgreens.com ©2021 Walgreen Co.

††This product is not manufactured or distributed by GlaxoSmithKline, the distributor of TUMS®.